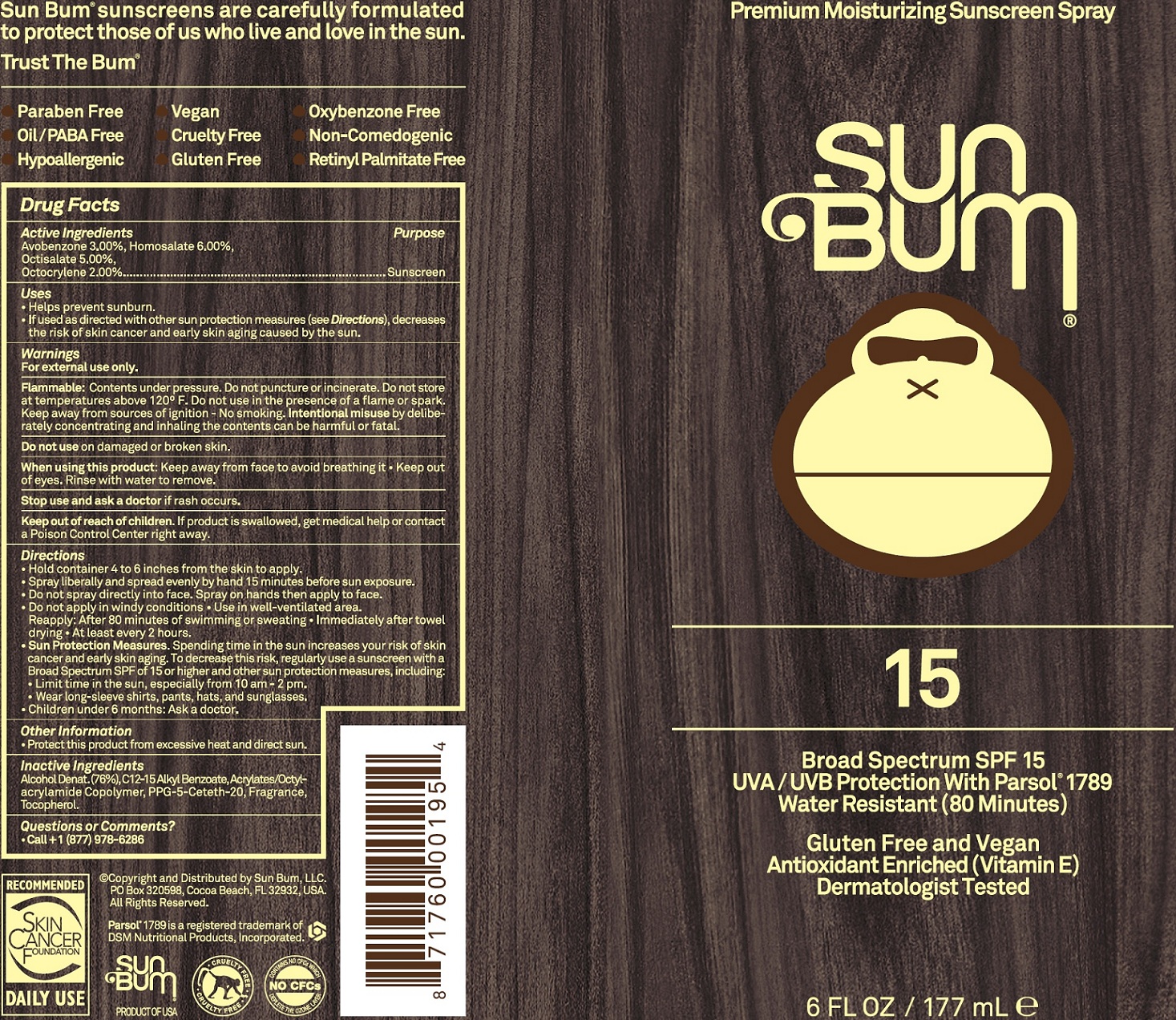 DRUG LABEL: Sun Bum SPF 15 Premium Moisturizing Sunscreen
NDC: 69039-224 | Form: SPRAY
Manufacturer: Sun Bum, LLC
Category: otc | Type: HUMAN OTC DRUG LABEL
Date: 20241021

ACTIVE INGREDIENTS: AVOBENZONE 30 mg/1 mL; HOMOSALATE 60 mg/1 mL; OCTISALATE 50 mg/1 mL; OCTOCRYLENE 20 mg/1 mL
INACTIVE INGREDIENTS: ALCOHOL; ALKYL (C12-15) BENZOATE; PPG-5-CETETH-20; TOCOPHEROL

Sun Bum SPF 15 Premium Moisturizing Sunscreen (Spray)

Active Ingredients

Avobenzone 3.00%, Homosalate 6.00%,

Octisalate 5.00%, Octocrylene 2.00%

Purpose

Sunscreen

Uses

- Helps prevent sunburn.
- If used as directed with other sun protection measures (see Directions), decreases the risk of skin cancer and early skin aging caused by the sun.

Warnings

Flammable: Contents under pressure. Do not puncture or inciinerate. Do not store at temperatures above 120°F. Do not use in the presence of a flame or spark keep away from sources of ignition - No smoking. Intentional misuse by deliberately concentrating and inhaling the contents can be harmful or fatal.

Do not use

on damaged or broken skin.

When using this product:

Keep away from face to avoid breathing it. Keep out of eyes. Rinse with water to remove.

Stop use and ask a doctor

if rash occurs.

Keep out of reach of children .

If product is swallowed, get medical help or contact a Poison Control Center right away.

Directions

- Hold container 4 to 6 inches from the skin to apply.
- Spray liberally and spread evenly by hand 15 minutes before sun exposure.
- Do not spray directly into face. Spray on hands then apply to face.
- Do not apply in windy conditions. Use in well-ventilated area.
- Reapply: After 80 minutes of swimming or sweating.
- Immediately after towel drying.
- At least every 2 hours.
- Sun Protection Measures. Spending time in the sun increases your risk of skin cancer and early skin aging, To decrease this risk, regularly use a sunscreen with a Broad Spectrum SPF of 15 or higher and other sun protection measures, including:
- Limit time in the sun, especially from 10 am - 2 pm.
- Wear long-sleeve shirts, pants, hats, and sunglasses.
- Children under 6 months: Ask a doctor.

Other Information

- Protect this product from excessive heat and direct sun.

Inactive Ingredients

Alcohol Denat.(76%), C12-15 Alkyl Benzoate, Acrylates/Octylacrylamide Copolymer, PPG-5-Ceteth-20, Fragrance, Tocopherol

Questions or Comments?

Call +1 (877) 978-6286